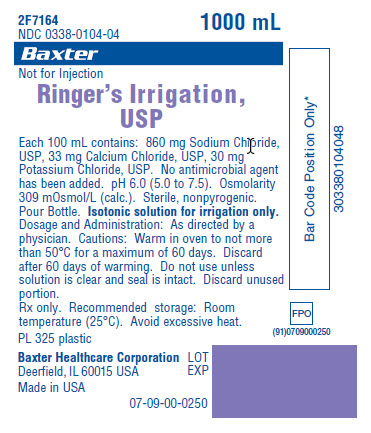 DRUG LABEL: Ringers
NDC: 0338-0104 | Form: IRRIGANT
Manufacturer: Baxter Healthcare Corporation
Category: prescription | Type: HUMAN PRESCRIPTION DRUG LABEL
Date: 20120613

ACTIVE INGREDIENTS: SODIUM CHLORIDE 860 mg/100 mL; CALCIUM CHLORIDE 33 mg/100 mL; POTASSIUM CHLORIDE 30 mg/100 mL
INACTIVE INGREDIENTS: WATER

DESCRIPTION

Ringer’s Irrigation, USP

Each 100 mL contains: 860 mg Sodium Chloride, USP, 33 mg Calcium Chloride, USP, 30 mg Potassium Chloride, USP. No antimicrobial agent has been added. pH 6.0 (5.0 to 7.5). Osmolarity 309 mOsmol/L (calc.). Sterile, nonpyrogenic. Pour Bottle.

INDICATIONS AND USAGE

Isotonic solution for irrigation only. Not for injection.

DOSAGE AND ADMINISTRATION

As directed by a physician.

Cautions: Warm in oven to not more than 50°C for a maximum of 60 days. Discard after 60 days of warming. Do not use unless solution is clear and seal is intact. Discard unused portion. Rx only.

HOW SUPPLIED

Recommended storage: Room temperature (25°C). Avoid excessive heat.

PRINCIPAL DISPLAY PANEL - PACKAGING LABELING

Container Label

Container Label

2F7164
NDC 0338-0104-04
1000 mL

Baxter Logo

Not for Injection

Ringer's Irrigation, USP

Each 100 mL contains: 860 mg Sodium Chloride,
USP, 33 mg Calcium Chloride, USP, 30 mg
Potassium Chloride, USP. No antimicrobial agent
has been added. pH 6.0 (5.0 to 7.5). Osmolarity
309 mOsmol/L (calc.). Sterile, nonpyrogenic.
Pour Bottle. Isotonic solution for irrigation only.
Dosage and Administration: As directed by a
physician. Cautions: Warm in oven to not more
than 50°C for a maximum of 60 days. Discard
after 60 days of warming. Do not use unless
solution is clear and seal is intact. Discard unused
portion.
Rx only. Recommended storage: Room
temperature (25°C). Avoid excessive heat.

PL 325 plastic

Baxter Healthcare Corporation
Deerfield, IL 60015 USA

Made in USA

07-09-00-0250

Bar Code Position Only*
303380104048

LOT
EXP